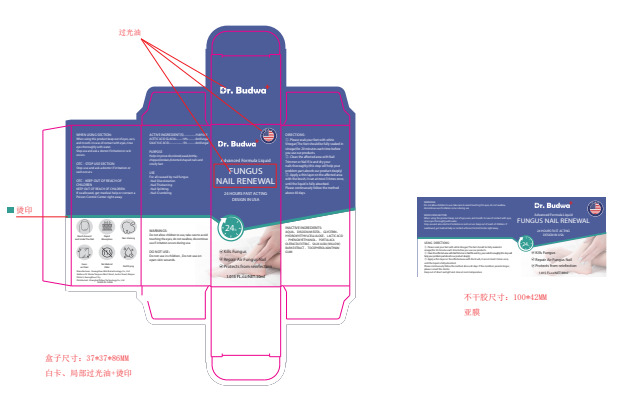 DRUG LABEL: Fungal Nail Liquid
NDC: 84251-001 | Form: LIQUID
Manufacturer: Shanghai DiGuo Technology Co., Ltd
Category: otc | Type: HUMAN OTC DRUG LABEL
Date: 20240408

ACTIVE INGREDIENTS: ACETIC ACID 10 g/100 mL; SALICYLIC ACID 5 g/100 mL
INACTIVE INGREDIENTS: TOCOPHEROL; SALIX ALBA BARK; XANTHAN GUM; HYDROXYETHYL CELLULOSE, UNSPECIFIED; LACTIC ACID; GLYCERIN; WATER; EDETATE DISODIUM; PHENOXYETHANOL

84251-001

Use

For all caused by nail fungus

Nail Discoloration

Nail Thickening

Nail Slitting

Nail Crumbling

Warnings

Do not allow children to use, take care to avoid touching the eyes, do not swallow, discontinue use if rritation occurs during use.

Do not use in children , Do not use on open skin wounds.

When using this product keep out of eyes, ears,and mouth. In case of contact with eyes, rinse eyes thoroughly with water.Stop use and ask a doctor if iritation or rash occurs.

Stop use and ask a doctor if irritation or rash occurs.

KEEP OUT OF REACH OF CHILDREN

KEEP OUT OF REACH OF CHIL .DREN:If swallowed, get medical help or contact a Poison Control Center right away.

Directions

①. Please soak your feet with white Vinegar(The feet should be fully soaked in vinegar)for 20 minutes each time before you use our products.

②. Clean the affected area with Nail Trimmer or Nail f le and dry your nails thoroughly.(this step will help your problem part absorb our product deeply)

③. Apply a thin layer on the affected area with the brush, it can at most 3 times once, until the liquid is fully absorbed. Please continuously follow the method above 40 days.

Other information

- Store between 15-30C (59-86F)
- Avoid freezing and excessive heat above 40C (104F)

Inactive ingredients

AQUA、DISODIUM EDTA、GLYCERIN. HYDROXYETHYLCELLUL OSE、LACTIC ACID、PHENOXYETHANOL、PORTULACA OLERACEA EXTRAC. SALIX ALBA (WILLOW) BARK EXTRACT、TOCOPHEROLXANTHAN GUM

PURPOSE

Helps improve discolored,weak bittle chipped,broken,distorted shaped nails and smelly feet